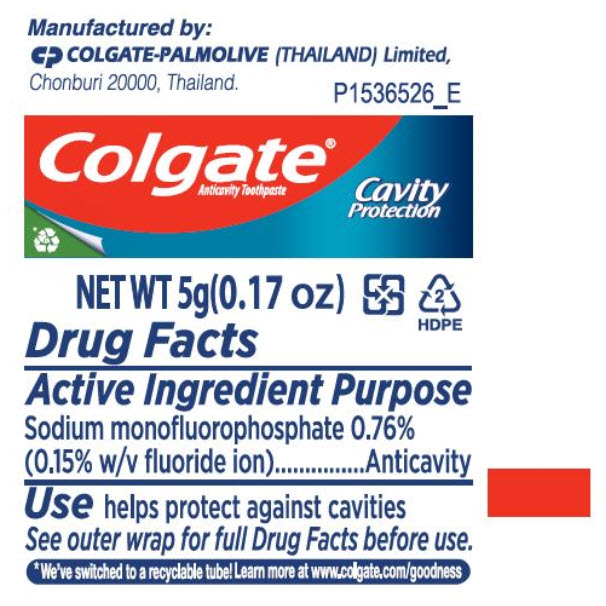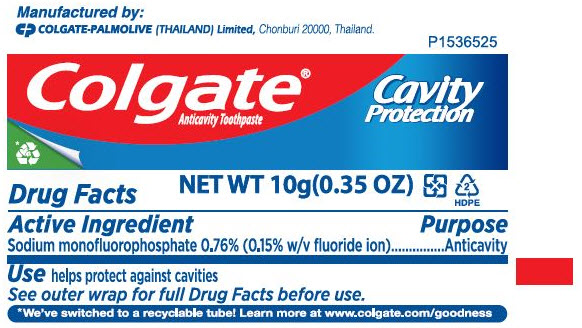 DRUG LABEL: Colgate Anticavity
NDC: 42555-060 | Form: PASTE, DENTIFRICE
Manufacturer: Colgate-Palmolive (Thailand) Limited - Branch
Category: otc | Type: HUMAN OTC DRUG LABEL
Date: 20241209

ACTIVE INGREDIENTS: SODIUM MONOFLUOROPHOSPHATE 7.6 mg/1 g
INACTIVE INGREDIENTS: DIBASIC CALCIUM PHOSPHATE DIHYDRATE; WATER; SORBITOL; SODIUM LAURYL SULFATE; CARBOXYMETHYLCELLULOSE SODIUM, UNSPECIFIED; SODIUM PYROPHOSPHATE; SACCHARIN SODIUM

Colgate® Anticavity Toothpaste

Drug Facts

Active ingredient

Sodium monofluorophosphate 0.76% (0.15% w/v fluoride ion)

Purpose

Anticavity

Use

helps protect against cavities

Warnings

KEEP OUT OF REACH OF CHILDREN

Keep out of the reach of children under 6 years of age. If more than used for brushing is accidentally swallowed, get medical help or contact a Poison Control Center right away.

Directions

adults and children 2 years of age and older | brush teeth thoroughly, preferably after each meal or at least twice a day, or as directed by a dentist or physician
children 2 to 6 years | use only a pea sized amount and supervise child's brushing and rinsing (to minimize swallowing)
children under 2 years | ask a dentist or physician

Inactive ingredients

dicalcium phosphate dihydrate, water, sorbitol, sodium lauryl sulfate, flavor, cellulose gum, tetrasodium pyrophosphate, sodium saccharin

Questions or comments?

Call toll-free 1-800-468-6502

Manufactured by:
COLGATE-PALMOLIVE (THAILAND) Limited,
Chonburi 20000, Thailand.

PRINCIPAL DISPLAY PANEL - 5 g Tube Label

P1536526_E

Colgate®
Anticavity Toothpaste

Cavity
Protection

NET WT 5g(0.17 oz)

2
HDPE

PRINCIPAL DISPLAY PANEL - 10 g Tube Label

P1536525

Colgate®
Anticavity Toothpaste

Cavity
Protection

NET WT 10g(0.35 OZ)

2
HDPE